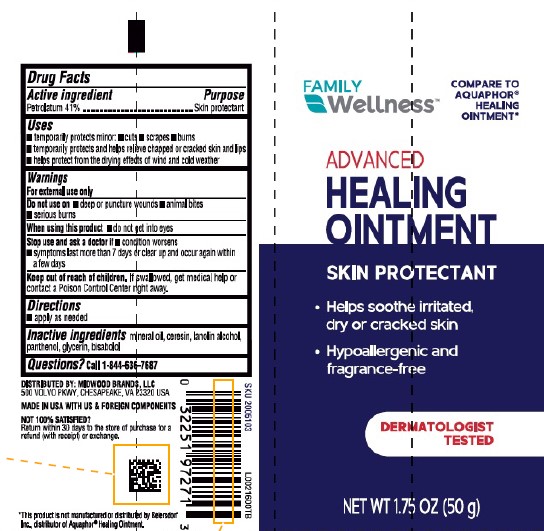 DRUG LABEL: Advanced Healing
NDC: 55319-952 | Form: OINTMENT
Manufacturer: Family Dollar Stores, Inc
Category: otc | Type: HUMAN OTC DRUG LABEL
Date: 20260224

ACTIVE INGREDIENTS: PETROLATUM 410 mg/1 g
INACTIVE INGREDIENTS: MINERAL OIL; CERESIN; LANOLIN ALCOHOLS; PANTHENOL; GLYCERIN; LEVOMENOL

Family Wellness 247.000/247AC
Healing Ointment for Dry and Cracked Skin

Active ingredient

Petrolatum 41%

Purpose

Skin protectant

Uses

- temporarily protects minor: cuts, scrapes, burns
- temporarily protects and helps relieve chapped or cracked skin and lips
- helps protect from the drying effects of wind and cold weather

Warnings

For external use only

Do not use on

- deep or puncture wounds
- animal bites
- serious burns

When using this product

- do not get in eyes

Stop use and ask a doctor if

- condition worsens
- symptoms last more than 7 days or clear up and occur again within a few days

Keep out of reach of children.

If swallowed, get medical help or contract a Poison Control Center right away.

Directions

- apply as needed

Inactive ingredients

mineral oil, ceresin, lanolin alcohol, panthenol, glycerin, bisabolol

Questions?

Call 1-844-636-7687

Disclaimer

*This product is not manufactured or distributed by Beiersdorf Inc., distributor Aquaphor® Healing Ointment.

Adverse reactions

DISTRIBUTED BY: MIDWOOD BRANDS, LLC

500 VOLVO PKWY, CHESAPEAKE, VA 23320 USA

MADE IN USA WITH US & FOREIGN COMPONENTS

NOT 100% SATISFIED? Return within 30 days to the store of purchase for a refund (with receipt) or exchange.

Principal display panel

FAMILY Wellness™

COMPARE TO AUQAPHOR® HEALING OINTMENT*

ADVANCED HEALING OINTMENT

SKIN PROTECTANT

- Helps soothe irritated, dry or cracked skin
- Hypoallergenic and fragrance-free

DERMATOLOGIST TESTED

NET WT 1.75 OZ (50 g)